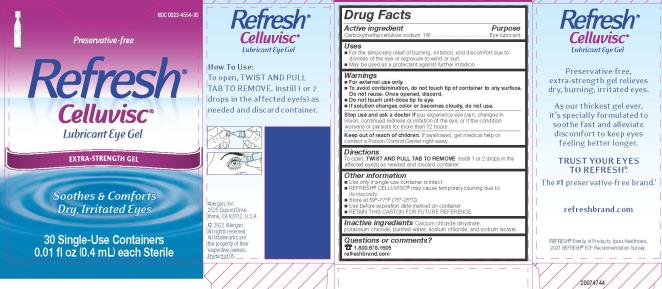 DRUG LABEL: REFRESH CELLUVISC
NDC: 0023-4554 | Form: GEL
Manufacturer: Allergan, Inc.
Category: otc | Type: HUMAN OTC DRUG LABEL
Date: 20220826

ACTIVE INGREDIENTS: CARBOXYMETHYLCELLULOSE SODIUM 10 mg/1 mL
INACTIVE INGREDIENTS: CALCIUM CHLORIDE; POTASSIUM CHLORIDE; WATER; SODIUM CHLORIDE; SODIUM LACTATE

REFRESH® CELLUVISC®
Drug Facts

Active ingredient

Carboxymethylcellulose sodium 1%

Purpose

Eye lubricant

Uses

- For the temporary relief of burning, irritation, and discomfort due to dryness of the eye or exposure to wind or sun.
- May be used as a protectant against further irritation.

Warnings

- For external use only.
- To avoid contamination, do not touch tip of container to any surface. Do not reuse. Once opened, discard.
- Do not touch unit-dose tip to eye.
- If solution changes color or becomes cloudy, do not use.

Stop use and ask a doctor if

you experience eye pain, changes in vision, continued redness or irritation of the eye, or if the condition worsens or persists for more than 72 hours.

Keep out of reach of children.

If swallowed, get medical help or contact a Poison Control Center right away.

Directions

To open, TWIST AND PULL TAB TO REMOVE. Instill 1 or 2 drops in the affected eye(s) as needed and discard container.

Other information

- Use only if single-use container is intact.
- REFRESH® CELLUVISC® may cause temporary blurring due to its viscosity.
- Store at 59°-77°F (15°-25°C).
- Use before expiration date marked on container.
- RETAIN THIS CARTON FOR FUTURE REFERENCE.

Inactive ingredients

Calcium chloride dihydrate; potassium chloride; purified water; sodium chloride; and sodium lactate.

Questions or comments?

1.800.678.1605

refreshbrand.com

v1.0DFL4554

PRINCIPAL DISPLAY PANEL

NDC 0023-4554-30
Preservative-free
Refresh®
Celluvisc®
Lubricant Eye Gel
EXTRA-STRENGTH GEL
Soothes & Comforts
Dry, Irritated Eyes30 Single-Use Containers
0.01 fl oz (0.4 mL) each Sterile